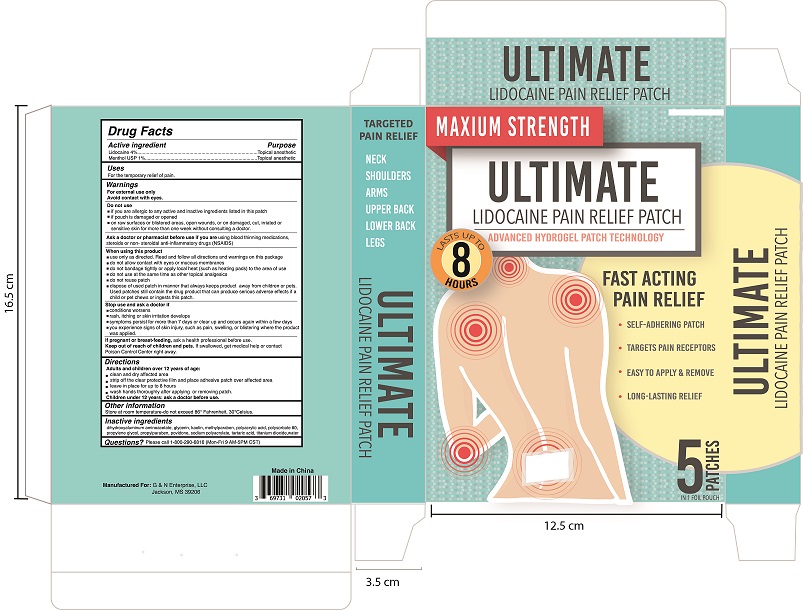 DRUG LABEL: Lidocaine Pain Relief Patch
NDC: 69159-920 | Form: PATCH
Manufacturer: Foshan Aqua Gel Biotech Co.,Ltd.
Category: otc | Type: HUMAN OTC DRUG LABEL
Date: 20171106

ACTIVE INGREDIENTS: MENTHOL, UNSPECIFIED FORM 1 g/100 g; LIDOCAINE 4 g/100 g
INACTIVE INGREDIENTS: POLYACRYLIC ACID (250000 MW); DIHYDROXYALUMINUM AMINOACETATE; GLYCERIN; KAOLIN; METHYLPARABEN; POLYSORBATE 80; PROPYLPARABEN; WATER; POVIDONE, UNSPECIFIED; SODIUM POLYACRYLATE (2500000 MW); PROPYLENE GLYCOL; TARTARIC ACID; TITANIUM DIOXIDE

Lidocaine Pain Relief Patch

Active Ingredients

Lidocaine 4%

Menthol 1%

Purpose:

Topical anesthetic

Topical anesthetic

Uses:

For the temporary relief of pain.

Warnings

For external use only
Avoid contact with eyes.

Do not use

- if you are allergic to any active and inactive ingredients listed in this patch
- if pouch is damaged or opened
- on raw surfaces or blistered areas, open wounds, or on damaged, cut, irriated or sensitive skin
- for more than one week without consulting a doctor.

When using this product

- use only as directed. Read and follow all directions and warnings on this package
- do not allow contact with eyes or mucous membranes
- do not bandage tightly or apply local heat (such as heating pads) to the area of use
- do not use at the same time as other topical analgesics
- do not reuse patch
- dispose of used patch in manner that always keeps product away from children or pets. Used patches still contain the drug product that can produce serious adverse effects if a child or pet chews or ingests this patch.

Stop use and ask a doctor if

- conditions worsens
- rash, itching or skin irritation develops
- symptoms persist for more than 7 days or clear up and occurs again within a few days
- you experience signs of skin injury, such as pain, swelling, or blistering where the product was applied.

If pregnant or breast feeding

ask a health professional before use.

Keep out of reach of children

If swallowed, get medical help or contact a Poison Control Center right away.

Directions

Adults and children over 12 years of age:

- clean and dry affected area
- strip off the clear protective film and place adhesive patch over affected area
- leave in place for up to 8 hours
- wash hands thoroughly after applying or removing patch.

Children under 12 years: ask a doctor before use.

Other Information

Store below 25°C (77°F). Avoid direct sunilght.

Inactive Ingredients:

dihydroxyaluminum aminoacetate, glycerin,kaolin,methylparaben,polyacrylic acid,polysorbate 80,propylene glycol,propylparaben, povidone,sodium polyacrylate, tartaric acid,tatanium dioxide,water.

Questions or Comments?

Please call 1-800-290-6816 (Mon-Fri 9AM-5PM CST)

Dosage and Administration

Lidocaine Pain Relief Patch contains 4% Lidocaine and 1% Menthol.